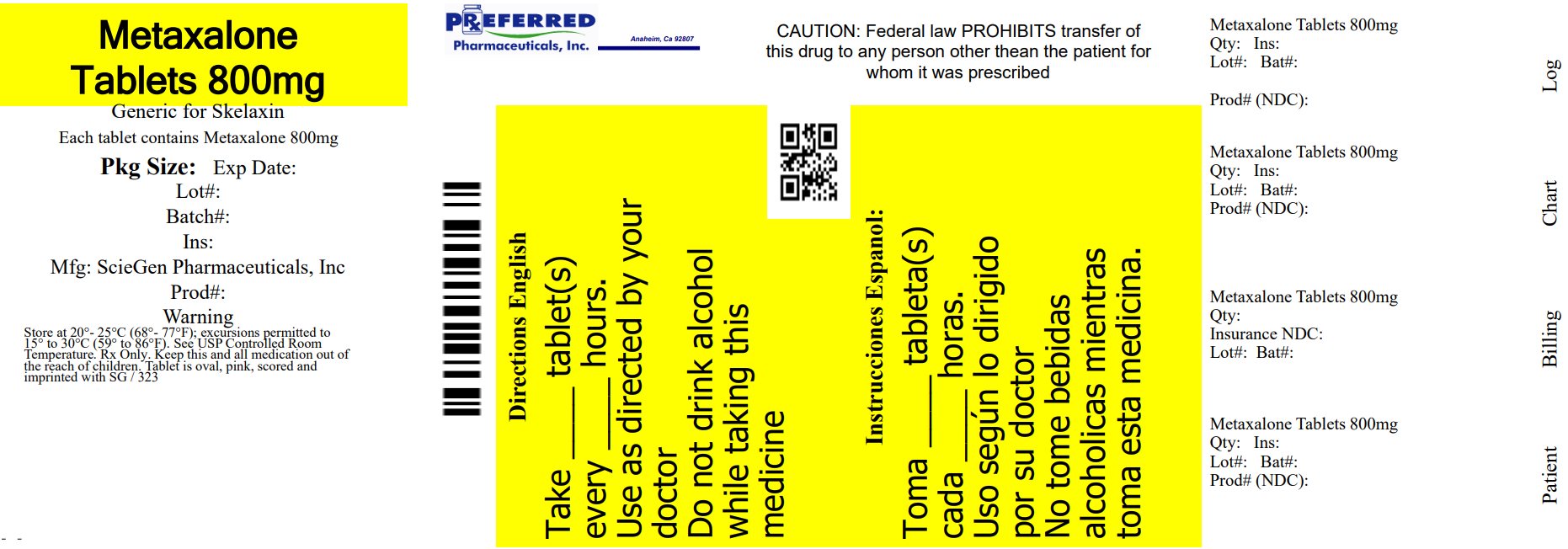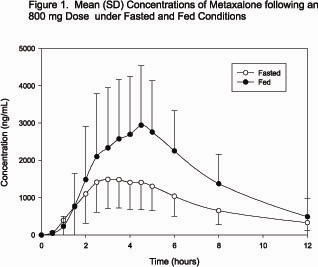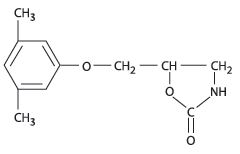 DRUG LABEL: Metaxalone
NDC: 68788-8678 | Form: TABLET
Manufacturer: Preferred Pharmaceuticals Inc.
Category: prescription | Type: HUMAN PRESCRIPTION DRUG LABEL
Date: 20251009

ACTIVE INGREDIENTS: METAXALONE 800 mg/1 1
INACTIVE INGREDIENTS: ALGINIC ACID; STARCH, CORN; FERRIC OXIDE RED; COPOVIDONE K25-31; MAGNESIUM STEARATE; POVIDONE, UNSPECIFIED; SODIUM ALGINATE

METAXALONE TABLETS, USP

DESCRIPTION

Metaxalone Tablets, USP are available as an 800 mg, capsule shaped, scored pink tablet. Chemically, metaxalone, USP is 5-[(3,5-dimethylphenoxy)methyl]-2-oxazolidinone. The empirical formula is C 12H 15NO 3, which corresponds to a molecular weight of 221.25. The structural formula is:

Metaxalone, USP is a white to almost white, crystalline powder freely soluble in dichloromethane, soluble in methanol, sparingly soluble in ethanol and ethyl acetate, slightly soluble in toluene and isopropanol, insoluble in water and n-hexane.

Each tablet contains 800 mg metaxalone, USP and the following inactive ingredients: alginic acid, corn starch, ferric oxide red, copovidone, magnesium stearate, povidone, pregelatinized starch, sodium alginate.

CLINICAL PHARMACOLOGY

Mechanism of Action:
The mechanism of action of metaxalone in humans has not been established, but may be due to general central nervous system (CNS) depression. Metaxalone has no direct action on the contractile mechanism of striated muscle, the motor end plate, or the nerve fiber.

Pharmacokinetics:
The pharmacokinetics of metaxalone have been evaluated in healthy adult volunteers after single dose administration of metaxalone under fasted and fed conditions at doses ranging from 400 mg to 800 mg.

Absorption
Peak plasma concentrations of metaxalone occur approximately 3 hours after a 400 mg oral dose under fasted conditions. Thereafter, metaxalone concentrations decline log-linearly with a terminal half-life of 9.0 ± 4.8 hours. Doubling the dose of metaxalone from 400 mg to 800 mg results in a roughly proportional increase in metaxalone exposure as indicated by peak plasma concentrations (C max) and area under the curve (AUC). Dose proportionality at doses above 800 mg has not been studied. The absolute bioavailability of metaxalone is not known.

The single-dose pharmacokinetic parameters of metaxalone in two groups of healthy volunteers are shown in Table 1.

Table 1: Mean (%CV) Metaxalone Pharmacokinetic Parameters
Dose (mg) | C max (ng/mL) | T max (h) | AUC ∞ (ng •h/mL) | t 1/2 (h) | CL/F (L/h)
400 ^1 | 983 (53) | 3.3 (35) | 7,479 (51) | 9.0 (53) | 68 (50)
800 ^2 | 1,816 (43) | 3.0 (39) | 15,044 (46) | 8.0 (58) | 66 (51)
^1Subjects received 1x400 mg tablet under fasted conditions (N=42)
^2Subjects received 2x400 mg tablets under fasted conditions (N=59)

Food Effects
A randomized, two-way, crossover study was conducted in 42 healthy volunteers (31 males, 11 females) administered one 400 mg metaxalone tablet under fasted conditions and following a standard high-fat breakfast. Subjects ranged in age from 18 to 48 years (mean age = 23.5 ± 5.7 years). Compared to fasted conditions, the presence of a high fat meal at the time of drug administration increased C max by 177.5% and increased AUC (AUC 0-t, AUC ∞) by 123.5% and 115.4%, respectively. Time-to-peak concentration (T max) was also delayed (4.3 h versus 3.3 h) and terminal half-life was decreased (2.4 h versus 9.0 h) under fed conditions compared to fasted.

In a second food effect study of similar design, two 400 mg metaxalone tablets (800 mg) were administered to healthy volunteers (N=59, 37 males, 22 females), ranging in age from 18 to 50 years (mean age = 25.6± 8.7 years). Compared to fasted conditions, the presence of a high fat meal at the time of drug administration increased C max by 193.6% and increased AUC (AUC 0-t, AUC ∞) by 146.4% and 142.2%, respectively. Time-to-peak concentration (T max) was also delayed (4.9 h versus 3.0 h) and terminal half-life was decreased (4.2 h versus 8.0 h) under fed conditions compared to fasted conditions. Similar food effect results were observed in the above study when one metaxalone 800 mg tablet was administered in place of two metaxalone 400 mg tablets. The increase in metaxalone exposure coinciding with a reduction in half-life may be attributed to more complete absorption of metaxalone in the presence of a high fat meal (Figure 1).

Distribution, Metabolism, and Excretion
Although plasma protein binding and absolute bioavailability of metaxalone are not known, the apparent volume of distribution (V/F ~ 800 L) and lipophilicity (log P = 2.42) of metaxalone suggest that the drug is extensively distributed in the tissues. Metaxalone is metabolized by the liver and excreted in the urine as unidentified metabolites. Hepatic Cytochrome P450 enzymes play a role in the metabolism of metaxalone. Specifically, CYP1A2, CYP2D6, CYP2E1, and CYP3A4 and, to a lesser extent, CYP2C8, CYP2C9, and CYP2C19 appear to metabolize metaxalone.

Metaxalone does not significantly inhibit major CYP enzymes such as CYP1A2, CYP2A6, CYP2B6, CYP2C8, CYP2C9, CYP2C19, CYP2D6, CYP2E1, and CYP3A4. Metaxalone does not significantly induce major CYP enzymes such as CYP1A2, CYP2B6, and CYP3A4 in vitro.

Pharmacokinetics in Special Populations

Age:
The effects of age on the pharmacokinetics of metaxalone were determined following single administration of two 400 mg tablets (800 mg) under fasted and fed conditions. The results were analyzed separately, as well as in combination with the results from three other studies. Using the combined data, the results indicate that the pharmacokinetics of metaxalone are significantly more affected by age under fasted conditions than under fed conditions, with bioavailability under fasted conditions increasing with age.

The bioavailability of metaxalone under fasted and fed conditions in three groups of healthy volunteers of varying age is shown in Table 2.

Table 2: Mean (%CV) Pharmacokinetic Parameters Following Single Administration of Two 400 mg Metaxalone Tablets (800 mg) under Fasted and Fed Conditions
 | Younger Volunteers |  | Older Volunteers
Age (years) | 25.6 ± 8.7 |  | 39.3 ± 10.8 |  | 71.5 ± 5.0
N | 59 |  | 21 |  | 23
Food | Fasted | Fed | Fasted | Fed | Fasted | Fed
C max (ng/mL) | 1,816 (43) | 3,510 (41) | 2,719 (46) | 2,915 (55) | 3,168 (43) | 3,680 (59)
T max (h) | 3.0 (39) | 4.9 (48) | 3.0 (40) | 8.7 (91) | 2.6 (30) | 6.5 (67)
AUC 0-t (ng•h/mL) | 14,531 (47) | 20,683 (41) | 19,836 (40) | 20,482 (37) | 23,797 (45) | 24,340 (48)
AUC ∞ (ng•h/mL) | 15,045 (46) | 20,833 (41) | 20,490 (39) | 20,815 (37) | 24,194 (44) | 24,704 (47)

Gender:
The effect of gender on the pharmacokinetics of metaxalone was assessed in an open label study, in which 48 healthy adult volunteers (24 males, 24 females) were administered two metaxalone 400 mg tablets (800 mg) under fasted conditions. The bioavailability of metaxalone was significantly higher in females compared to males as evidenced by C max (2,115 ng/mL versus 1,335 ng/mL) and AUC ∞ (17,884 ng•h/mL versus 10,328 ng•h/mL). The mean half-life was 11.1 hours in females and 7.6 hours in males. The apparent volume of distribution of metaxalone was approximately 22% higher in males than in females, but not significantly different when adjusted for body weight. Similar findings were also seen when the previously described combined dataset was used in the analysis.

Hepatic/Renal Insufficiency:
The impact of hepatic and renal disease on the pharmacokinetics of metaxalone has not been determined. In the absence of such information, metaxalone should be used with caution in patients with hepatic and/or renal impairment.

INDICATIONS AND USAGE

Metaxalone is indicated as an adjunct to rest, physical therapy, and other measures for the relief of discomforts associated with acute, painful musculoskeletal conditions. The mode of action of this drug has not been clearly identified, but may be related to its sedative properties. Metaxalone does not directly relax tense skeletal muscles in man.

CONTRAINDICATIONS

Known hypersensitivity to any components of this product.

Known tendency to drug induced, hemolytic, or other anemias.

Significantly impaired renal or hepatic function.

WARNINGS

Serotonin Syndrome
Cases of serotonin syndrome, a potentially life-threatening condition, have been reported during concomitant use of serotonergic drugs with metaxalone used within the recommended dosage range (see PRECAUTIONS: Drug Interactions) and with metaxalone as a single agent taken at doses higher than the recommended dose (see OVERDOSAGE). Serotonergic drugs include selective serotonin reuptake inhibitors (SSRIs), serotonin and norepinephrine reuptake inhibitors (SNRIs), tricyclic antidepressants (TCAs), triptans, 5-HT3 receptor antagonists, opioids (particularly fentanyl, meperidine, and methadone), drugs that affect the serotonergic neurotransmitter system (e.g., mirtazapine, trazodone, tramadol), and drugs that impair metabolism of serotonin (including monoamine oxidase (MAO) inhibitors, both those intended to treat psychiatric disorders and also others, such as linezolid and intravenous methylene blue) (see PRECAUTIONS: Drug Interactions).

Serotonin syndrome symptoms may include mental status changes (e.g., agitation, hallucinations, coma), autonomic instability (e.g., tachycardia, labile blood pressure, hyperthermia), neuromuscular aberrations (e.g., hyperreflexia, incoordination, rigidity), and/or gastrointestinal symptoms (e.g., nausea, vomiting, diarrhea). The onset of symptoms generally occurs within several hours to a few days, but may occur later than that. Discontinue metaxalone if serotonin syndrome is suspected.

Risks from Concomitant Use with Alcohol or other CNS Depressants
The sedative effects of metaxalone and other CNS depressants (e.g., alcohol, benzodiazepines, opioids, tricyclic antidepressants (TCAs)) may be additive. Exercise caution with patients who take more than one of these CNS depressants simultaneously. Follow patients closely for signs and symptoms of respiratory depression and sedation (see PRECAUTIONS: Drug Interactions).

PRECAUTIONS

Metaxalone should be administered with great care to patients with pre-existing liver damage. Serial liver function studies should be performed in these patients.

False-positive Benedict’s tests, due to an unknown reducing substance, have been noted. A glucose-specific test will differentiate findings.

Taking metaxalone with food may enhance general CNS depression; elderly patients may be especially susceptible to this CNS effect. (See CLINICAL PHARMACOLOGY: Pharmacokinetics and PRECAUTIONS: Information for Patients).

Information for Patients

Driving or Operating Heavy Machinery:
Metaxalone may impair mental and/or physical abilities required for performance of hazardous tasks, such as operating machinery or driving a motor vehicle, especially when used with alcohol or other CNS depressants.

Serotonin Syndrome:
Inform patients that metaxalone could cause a rare but potentially life-threatening condition resulting from administration of doses higher than the recommended dose or from concomitant administration of serotonergic drugs with metaxalone used within the recommended dosage range. Warn patients of the symptoms of serotonin syndrome and to seek medical attention right away if symptoms develop. Instruct patients to inform their healthcare providers if they are taking, or plan to take, serotonergic medications (see WARNINGS, PRECAUTIONS: Drug Interactions, and OVERDOSAGE).

Drug Interactions

CNS Depressants:
The sedative effects of metaxalone and other CNS depressants (e.g., alcohol, benzodiazepines, opioids, tricyclic antidepressants (TCAs)) may be additive. Exercise caution with patients who take more than one of these CNS depressants simultaneously. Follow patients closely for signs and symptoms of respiratory depression and sedation (see WARNINGS).

Serotonergic Drugs:
Serotonin syndrome has resulted from concomitant use of serotonergic drugs with metaxalone used within the recommended dosage range (see WARNINGS). If concomitant use is warranted, carefully observe the patient, particularly during treatment initiation and dose adjustment. Discontinue metaxalone if serotonin syndrome is suspected.

Examples of serotonergic drugs include: selective serotonin reuptake inhibitors (SSRIs), serotonin and norepinephrine reuptake inhibitors (SNRIs), tricyclic antidepressants (TCAs), triptans, 5-HT3 receptor antagonists, opioids (particularly fentanyl, meperidine, and methadone), drugs that affect the serotonin neurotransmitter system (e.g., mirtazapine, trazodone, tramadol), monoamine oxidase (MAO) inhibitors (those intended to treat psychiatric disorders and also others, such as linezolid and intravenous methylene blue).

Carcinogenesis, Mutagenesis, Impairment of Fertility

The carcinogenic potential of metaxalone has not been determined.

Pregnancy
Reproduction studies in rats have not revealed evidence of impaired fertility or harm to the fetus due to metaxalone. Post marketing experience has not revealed evidence of fetal injury, but such experience cannot exclude the possibility of infrequent or subtle damage to the human fetus. Safe use of metaxalone has not been established with regard to possible adverse effects upon fetal development. Therefore, metaxalone tablets should not be used in women who are or may become pregnant and particularly during early pregnancy unless, in the judgement of the physician, the potential benefits outweigh the possible hazards.

Nursing Mothers
It is not known whether this drug is secreted in human milk. As a general rule, nursing should not be undertaken while a patient is on a drug since many drugs are excreted in human milk.

Pediatric Use
Safety and effectiveness in children 12 years of age and below have not been established.

ADVERSE REACTIONS

The most frequent reactions to metaxalone include:

CNS: drowsiness, dizziness, headache, and nervousness or “irritability”;

Digestive: nausea, vomiting, gastrointestinal upset.

Other adverse reactions are:

Immune System: anaphylaxis, hypersensitivity reaction, rash with or without pruritus;

Hematologic: leukopenia; hemolytic anemia;

Hepatobiliary: jaundice.

CNS: cases of serotonin syndrome, a potentially life-threatening condition, have been reported during concomitant use of serotonergic drugs with metaxalone used within the recommended dosage range and with metaxalone as a single agent taken at doses higher than the recommended dose (see WARNINGS, PRECAUTIONS: Drug Interactions, and OVERDOSAGE).

To report SUSPECTED ADVERSE REACTIONS, contact Dr.Reddy’s Laboratories, Inc., at 1-888-375-3784 or FDA at 1-800-FDA-1088 or http://www.fda.gov/medwatch

OVERDOSAGE
Deaths by deliberate or accidental overdose have occurred with metaxalone, particularly in combination with antidepressants, and have been reported with this class of drug in combination with alcohol.

Serotonin syndrome has been reported when metaxalone was used at doses higher than the recommended dose (see WARNINGS and ADVERSE REACTIONS).

When determining the LD 50 in rats and mice, progressive sedation, hypnosis and finally respiratory failure were noted as the dosage increased. In dogs, no LD 50 could be determined as the higher doses produced an emetic action in 15 to 30 minutes.

Treatment - Gastric lavage and supportive therapy. Consultation with a regional poison control center is recommended.

DOSAGE AND ADMINISTRATION
The recommended dose for adults and children over 12 years of age is one 800 mg tablet three to four times a day.

HOW SUPPLIED

Metaxalone Tablets, USP 800 mg are available as pink, capsule shape scored tablet debossed with ‘SG’ on scored side and ‘323’ on the other.

NDC 68788-8678-9: Bottles of 90 Tablets

NDC 68788-8678-1: Bottles of 100 Tablets

Store at 20° to 25°C (68° to 77°F); excursions permitted to 15° to 30°C (59° to 86°F) [See USP Controlled Room Temperature]. Dispense in well-closed, light-resistant containers.

You can ask your pharmacist or doctor for information about Metaxalone Tablets USP, or call 1-888-375-3784.

Rx Only

Manufactured by:
ScieGen Pharmaceuticals, Inc.
Hauppauge, NY 11788, USA

Manufactured for:
Dr.Reddy’s Laboratories Inc.
Princeton, New Jersey 08540, USA
Rev: 06/20

Repackaged By: Preferred Pharmaceuticals Inc.

PRINCIPAL DISPLAY PANEL

NDC 68788-8678

This container is not intended for household use.

Metaxalone
Tablets, USP

800 mg

Rx Only

SEALED FOR YOUR PROTECTION

Dr.Reddy’s

Repackaged By: Preferred Pharmaceuticals Inc.